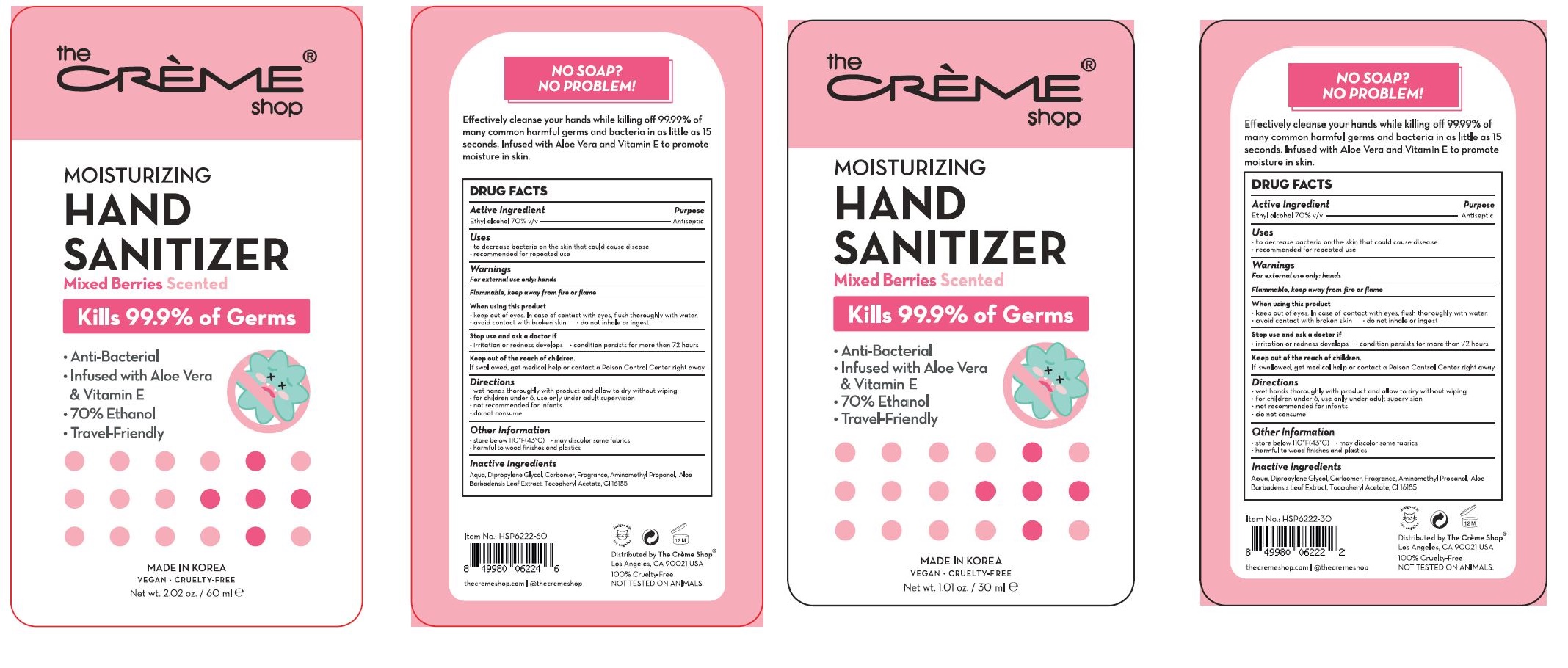 DRUG LABEL: The creme shop moisturizing hand sanitizer mixed berries
NDC: 74200-0013 | Form: GEL
Manufacturer: URBANBCL CO LTD
Category: otc | Type: HUMAN OTC DRUG LABEL
Date: 20220418

ACTIVE INGREDIENTS: ALCOHOL 70 mL/100 mL
INACTIVE INGREDIENTS: CARBOMER 940; WATER; DIPROPYLENE GLYCOL; .ALPHA.-TOCOPHEROL ACETATE; ALOE VERA LEAF; AMINOMETHYLPROPANOL

Drug Facts

ACTIVE INGREDIENT

ethyl alcohol

PURPOSE

The convenient Sense Fresh Advanced Instant Hand Sanitizer with Aloe is an antimicrobial liquid that contains 70 percent ethyl alcohol to help reduce the number of germs on hands, and three moisturizers to help keep skin hydrated. No rinsing with water or drying with towels is needed. Alcohol-based hand sanitizers can quickly reduce the number of germs on hands within 30 seconds. The hand sanitizer meets U.S. Food and Drug Administration (FDA) healthcare personnel hand-washing requirements. It’s perfect for on-the-go uses when traveling outside of the home, and fits neatly in purses, backpacks or briefcases.

KEEP OUT OF REACH OF THE CHILDREN

INDICATIONS AND USAGE

wet hands thoroughly with product and allow to dry without wiping

for children under 6, use only under adult supervision

not recommended for infants

do not consume

WARNINGS

■ Flammable. Keep away from fire or flame.

■ For external use only.

■ Do not use in eyes.

■ lf swallowed, get medical help promptly.

■ Stop use, ask doctor lf irritation occurs.

■ Keep out of reach of children.

DOSAGE AND ADMINISTRATION

for external use only

INACTIVE INGREDIENT

Aqua
Dipropylene Glycol
Carbomer
Fragrance
Aminomethyl Propanol
Aloe Barbadensis Leaf Extract
Tocopheryl Acetate
CI 16185